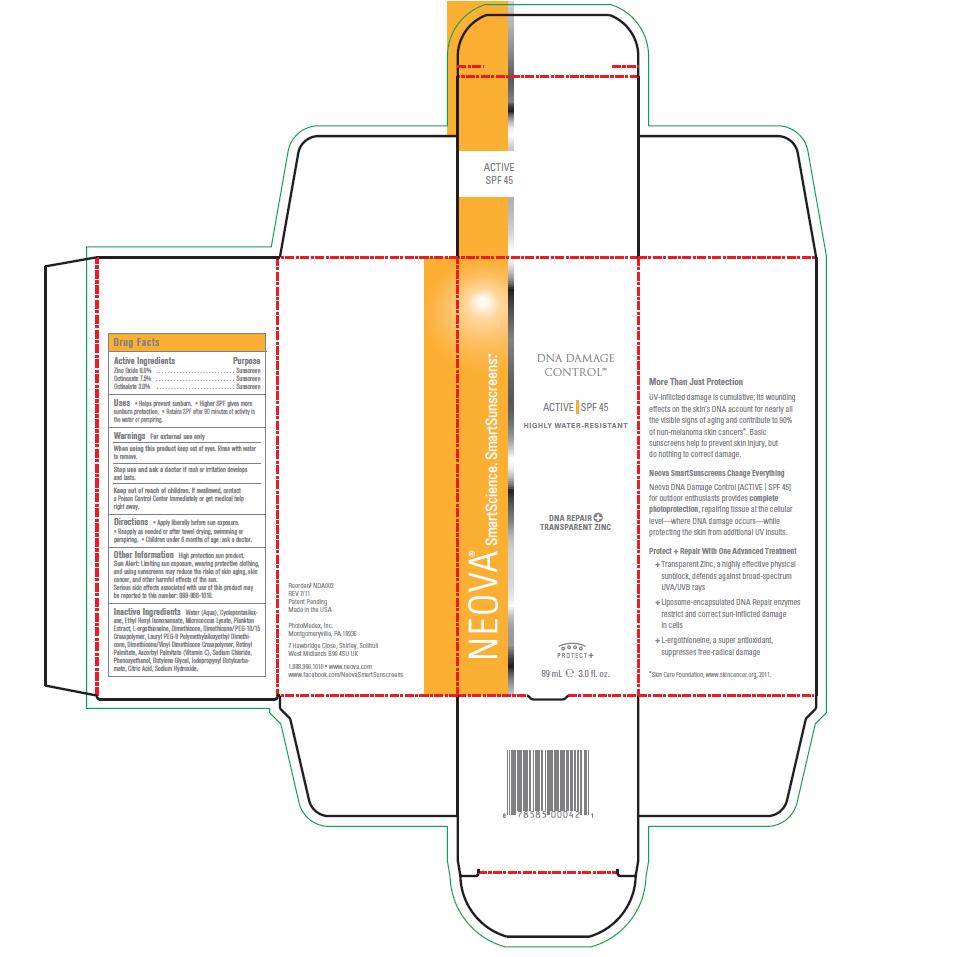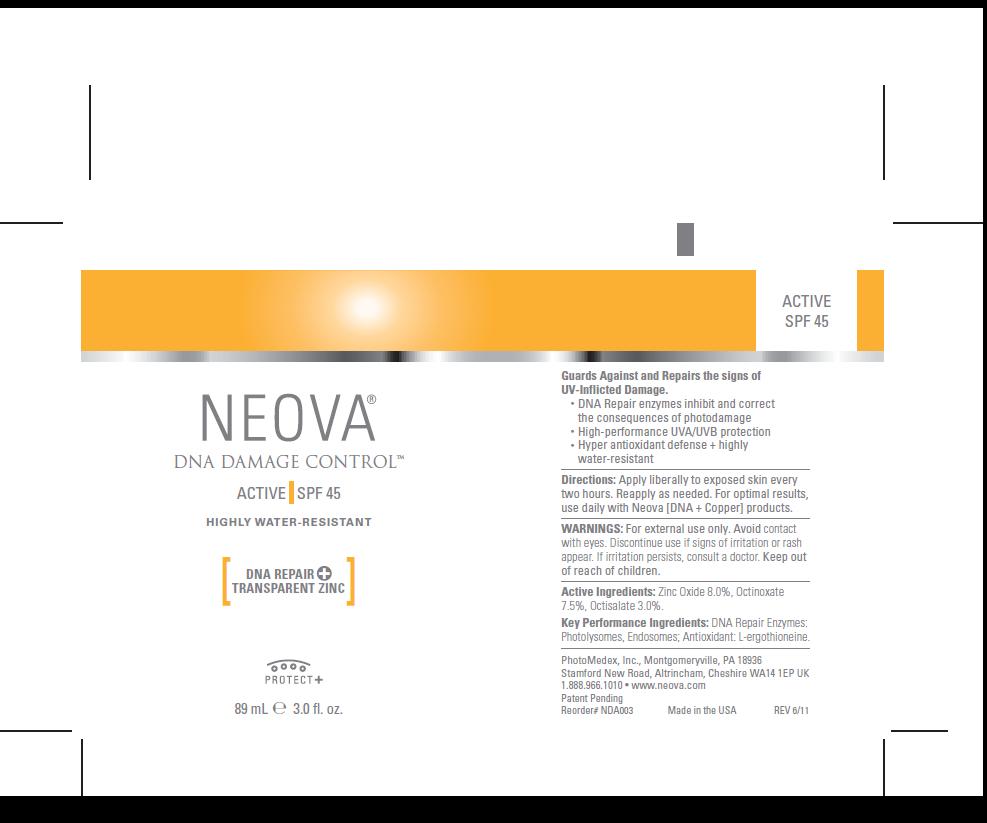 DRUG LABEL: Neova DNA Damage Control - Active
NDC: 62362-129 | Form: EMULSION
Manufacturer: PhotoMedex, Inc.
Category: otc | Type: HUMAN OTC DRUG LABEL
Date: 20120105

ACTIVE INGREDIENTS: Zinc Oxide 8 mL/100 mL; Octinoxate 7.5 mL/100 mL; Octisalate 3 mL/100 mL
INACTIVE INGREDIENTS: Water; Cyclomethicone 5; Ethylhexyl Isononanoate; Micrococcus Luteus; Ergothioneine; Dimethicone; Vitamin A Palmitate; Ascorbyl Palmitate; Sodium Chloride; Phenoxyethanol; Butylene Glycol; Iodopropynyl Butylcarbamate; Citric Acid; Sodium Hydroxide

Neova DNA Damage Control - Active SPF 45 - Drug Facts

Active Ingredients

Zinc Oxide 8.0%, Octinoxate 7.5%, Octisalate 3.0%

Purpose

Zinc Oxide - sunscreen, Octinoxate - sunscreen, Octisalate - sunscreen

Uses

• Helps prevent sunburn. • Higher SPF gives more
sunburn protection. • Retains SPF after 80 minutes of activity in
the water or perspiring.

Warnings

For external use only

When using this product

Keep out of eyes. Rinse with water to remove.

Stop use and ask a doctor if

Rash or irritation develops and lasts.

Keep out of reach of children

If swallowed, contact a Poison Control Center immediately or get medical help right away.

Directions

Apply liberally before sun exposure.
• Reapply as needed or after towel drying, swimming or perspiring. • Children under 6 months of age: ask a doctor.

Other Information

High protection sun product. Sun Alert: Limiting sun exposure, wearing protective clothing, and using sunscreens may reduce the risks of skin aging, skin cancer, and other harmful effects of the sun. Serious side effects associated with use of this product may be reported to this number: 888-966-1010.

Inactive Ingredients

Water (Aqua), Cyclopentasiloxane,
Ethyl Hexyl Isononanoate, Micrococcus Lysate, Plankton
Extract, L-ergothioneine, Dimethicone, Dimethicone/PEG-10/15
Crosspolymer, Lauryl PEG-9 Polymethylsiloxyethyl Dimethicone,
Dimethicone/Vinyl Dimethicone Crosspolymer, Retinyl
Palmitate, Ascorbyl Palmitate (Vitamin C), Sodium Chloride,
Phenoxyethanol, Butylene Glycol, Iodopropynyl Butylcarbamate,
Citric Acid, Sodium Hydroxide.